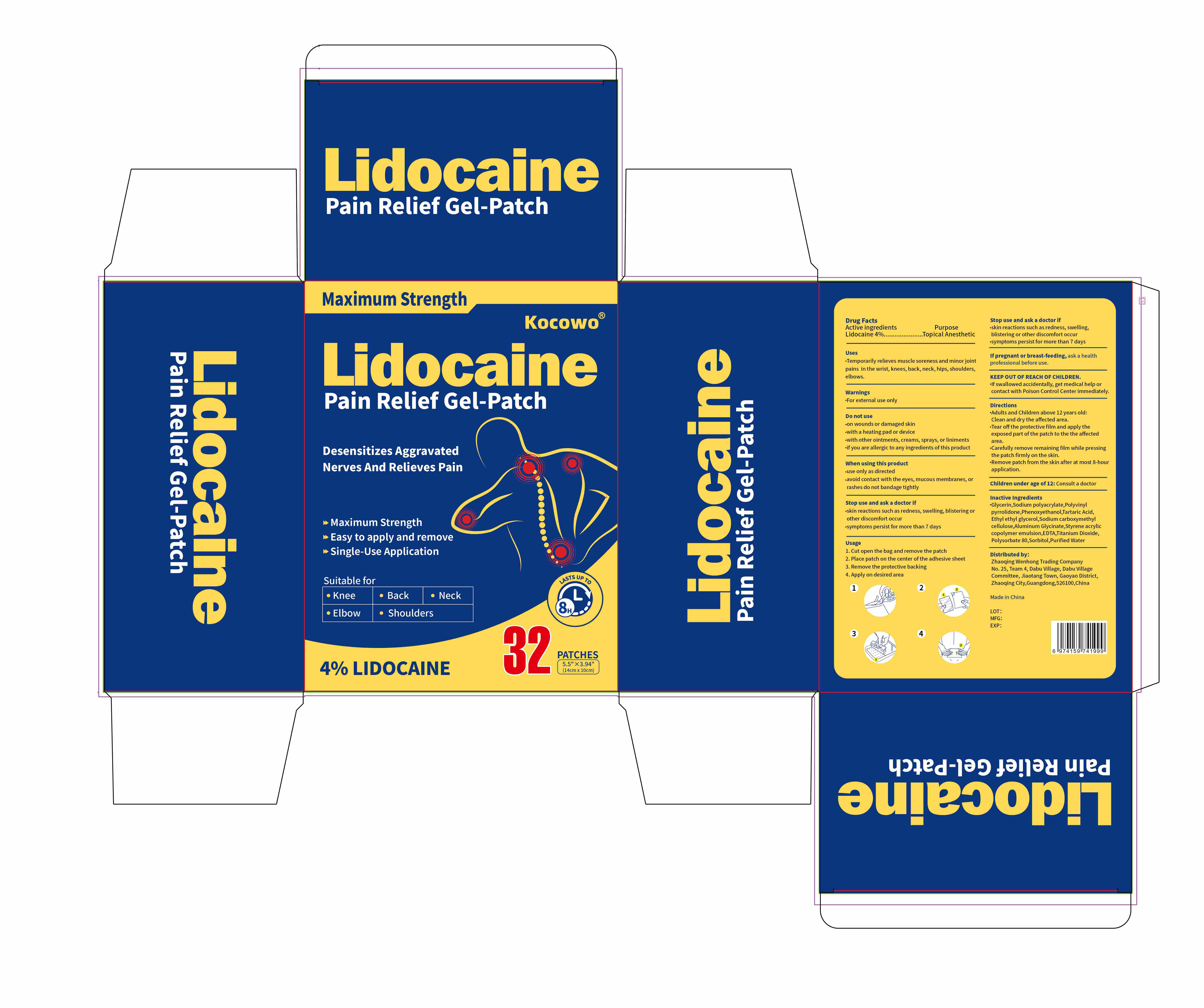 DRUG LABEL: Kocowo Lidocaine Pain Relief Gel-Patch
NDC: 83559-010 | Form: PATCH
Manufacturer: Henan Enokon Medical Instrument Co., Ltd.
Category: otc | Type: HUMAN OTC DRUG LABEL
Date: 20250803

ACTIVE INGREDIENTS: LIDOCAINE 4 g/100 1
INACTIVE INGREDIENTS: POLYSORBATE 80; GLYCERIN; ALUMINUM GLYCINATE; ETHYLHEXYLGLYCERIN; CARBOXYMETHYLCELLULOSE SODIUM; EDTA; WATER; SODIUM ACRYLATE; TITANIUM DIOXIDE; STYRENE/ACRYLAMIDE COPOLYMER (MW 500000); PHENOXYETHANOL; SORBITOL; TARTARIC ACID; POVIDONE

83559-010

Active Ingredient

Lidocaine 4%

Purpose

Topical anesthetic

Use

Temporarily relieves muscle soreness and minor joint pains in the wrist, knees, back, neck, hips, shoulders, elbows.

Warnings

For external use only

Do not use

on wounds or damaged skin
with a heating pad or device
with other ointments, creams, sprays, or liniments
if you are allergic to any ingredients of this product

When Using

use only as directed
avoid contact with the eyes, mucous membranes or rashes
do not bandage tightly

Stop Use

Stop use and ask a doctor if
skin reactions such as redness, swelling, blistering or other discomfort occur.
symptoms persist for more than 7 days

Ask Doctor

If pregnant or breast-feeding, ask a health professional before use.
Children under age of 12: Consult a doctor

Keep Out Of Reach Of Children

If swallowed accidentally, get medical help or contact with Poison Control Center immediately.

Directions

Adults and Children above 12 years old:
Clean and dry the affected area.
Tear off the protective film and apply the exposed part of the patch to the the affected area.
Carefully remove remaining film while pressing the patch firmly on the skin.
Remove patch from the skin after at most 8-hour application.

Inactive ingredients

Glycerin,Sodium polyacrylate,Polyvinyl pyrrolidone,Phenoxyethanol,Tartaric Acid,Ethyl ethyl glycerol,Sodium carboxymethyl cellulose,Aluminum Glycinate,Styrene acrylic copolymer emulsion,EDTA,Titanium Dioxide,Polysorbate 80,Sorbitol,Purified Water